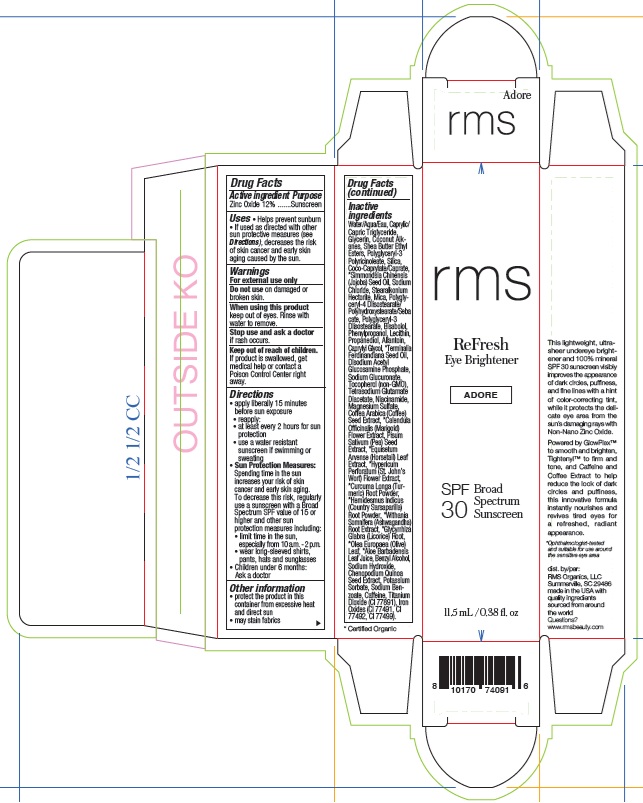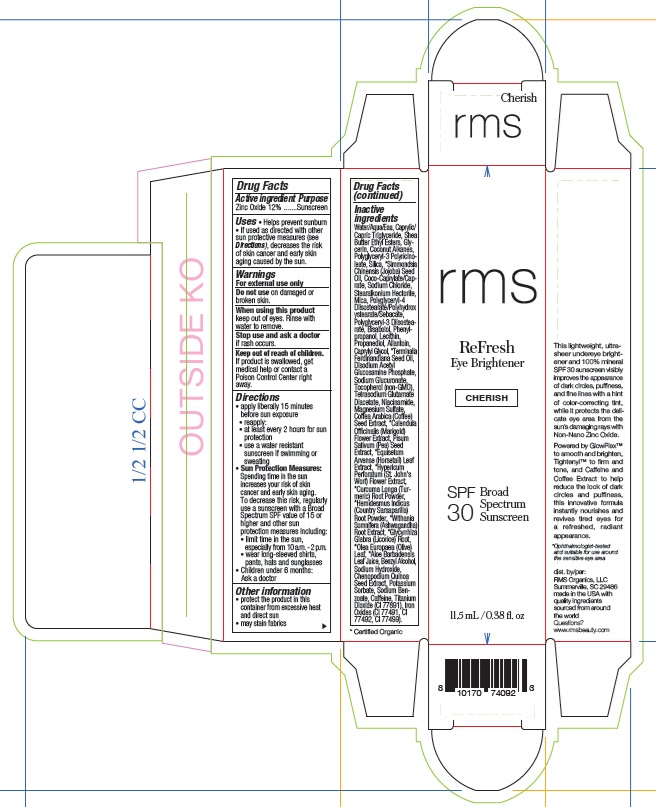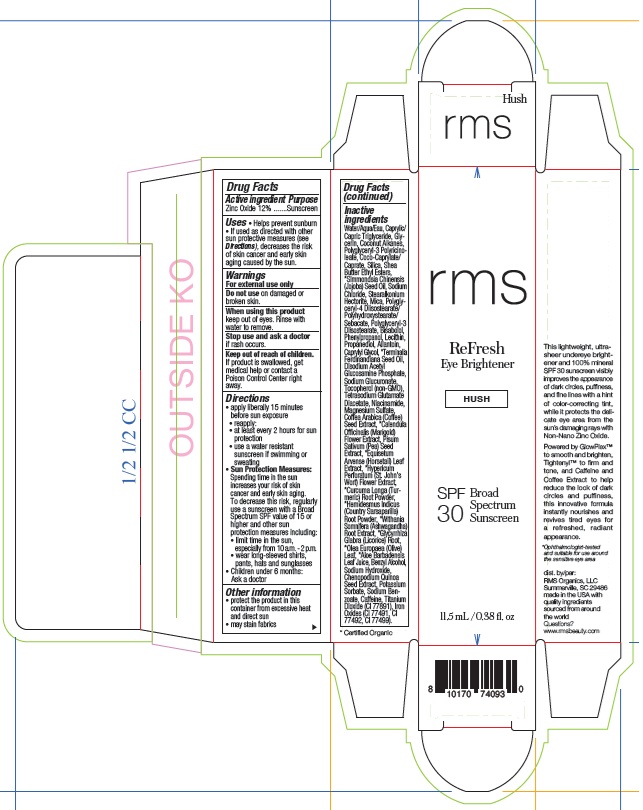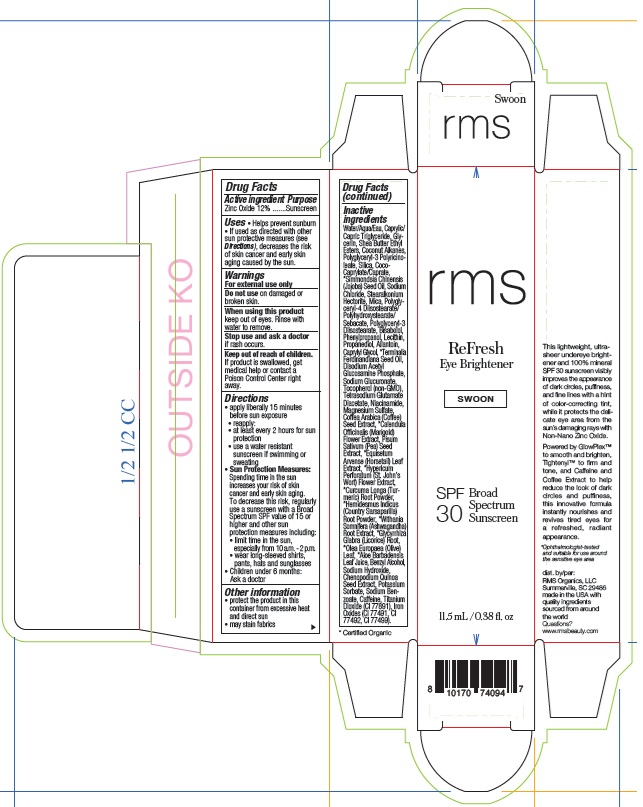 DRUG LABEL: RMS REFRESH EYE BRIGHTENER SPF 30 BROAD SPECTRUM SUNSCREEN ADORE
NDC: 83249-017 | Form: EMULSION
Manufacturer: Rms organics LLC
Category: otc | Type: HUMAN OTC DRUG LABEL
Date: 20250825

ACTIVE INGREDIENTS: ZINC OXIDE 120 mg/1 mL
INACTIVE INGREDIENTS: PEA; MAGNESIUM SULFATE, UNSPECIFIED; CAPRYLYL GLYCOL; NIACINAMIDE; MICA; TITANIUM DIOXIDE; FERRIC OXIDE RED; FERROSOFERRIC OXIDE; MEDIUM-CHAIN TRIGLYCERIDES; GLYCERIN; POTASSIUM SORBATE; WATER; SODIUM BENZOATE; BENZYL ALCOHOL; FERRIC OXIDE YELLOW; POLYGLYCERYL-4 DIISOSTEARATE/POLYHYDROXYSTEARATE/SEBACATE; COCO-CAPRYLATE/CAPRATE; SODIUM HYDROXIDE; TOCOPHEROL; SILICON DIOXIDE; LECITHIN, SUNFLOWER; TETRASODIUM GLUTAMATE DIACETATE; CHENOPODIUM QUINOA SEED; WITHANIA SOMNIFERA ROOT; COCONUT ALKANES; SHEA BUTTER ETHYL ESTERS; JOJOBA OIL; OLEA EUROPAEA (OLIVE) LEAF; CAFFEINE; HEMIDESMUS INDICUS ROOT; STEARALKONIUM HECTORITE; PHENYLPROPANOL; DISODIUM ACETYL GLUCOSAMINE PHOSPHATE; ARABICA COFFEE BEAN; HYPERICUM PERFORATUM FLOWER; ALOE VERA LEAF JUICE; SODIUM GLUCURONATE; POLYGLYCERYL-3 PENTARICINOLEATE; SODIUM CHLORIDE; PROPANEDIOL; CALENDULA OFFICINALIS FLOWER; EQUISETUM ARVENSE BRANCH; TURMERIC; GLYCYRRHIZA GLABRA (LICORICE) ROOT; LEVOMENOL; ALLANTOIN

RMS REFRESH EYE BRIGHTENER SPF 30 BROAD SPECTRUM SUNSCREEN

Active ingredient

Zinc Oxide 12%

Purpose

Sunscreen

Uses

- Helps prevent sunburn
- If used as directed with other sun protective measures (see Directions), decreases the risk of skin cancer and early skin aging caused by the sun.

Warnings

For external use only

Do not use

on damaged or broken skin.

When using this product

keep out of eyes. Rinse with water to remove.

Stop use and ask a doctor

if rash occurs.

Keep out of reach of children.

If product is swallowed, get medical help or contact a Poison Control Center right away.

Directions

- apply liberally 15 minutes before sun exposure
- reapply:
- at least every 2 hours for sun protection
- use a water resistant suncreen if swimming or sweating
- Sun Protection Measures: Spending time in the sun increases your risk of skin cancer and early skin aging. To decrease this risk, regularly use a sunscreen with a Broad Spectrum SPF value of 15 or higher and other sun protection measures including:
- limit tine in the sun, especially from 10 a.m. - 2 p.m.
- wear long-sleeved shirts, pants, hats and sunglasses
- Children under 6 months: Ask a doctor

Other information

- protect the product from excessive heat and direct sun
- may stain fabrics

Inactive ingredients

Adore

Water/Aqua/Eau, Caprylic/Capric Triglyceride, Glycerin, Coconut Alkanes, Shea Butter Ethyl Esters, Polyglyceryl-3 Polyricinoleate, Silica, Coco-Caprylate/Caprate, *Simmondsia Chinensis (Jojoba) Seed Oil, Sodium Chloride, Stearalkonium Hectorite, Mica, Polyglyceryl-4 Diisostearate/Polyhydroxystearate/Sebacate, Polyglyceryl-3 Diisostearate, Bisabolol, Phenylpropanol, Lecithin, Propanediol, Allantoin, Caprylyl Glycol, *Terminalia Ferdinandiana Seed Oil, Disodium Acetyl Glucosamine Phosphate, Sodium Glucuronate, Tocopherol (non-GMO), Tetrasodium Glutamate Diacetate, Niacinamide, Magnesium Sulfate, Coffea Arabica (Coffee) Seed Extract, *Calendula Officinalis (Marigold) Flower Extract, Pisum Sativum (Pea) Seed Extract, *Equisetum Arvense (Horsetail) Leaf Extract, *Hypericum Perforatum (St. John’s Wort) Flower Extract, *Curcuma Longa (Turmeric) Root Powder, *Hemidesmus Indicus (Country Sarsaparilla) Root Powder, *Withania Somnifera (Ashwagandha) Root Extract, *Glycyrrhiza Glabra (Licorice) Root, *Olea Europaea (Olive) Leaf, *Aloe Barbadensis Leaf Juice, Benzyl Alcohol, Sodium Hydroxide, Chenopodium Quinoa Seed Extract, Potassium Sorbate, Sodium Benzoate, Caffeine, Titanium Dioxide (CI 77891), Iron Oxides (CI 77491, CI 77492, CI 77499).

*Certified Organic

Cherish

Water/Aqua/Eau, Caprylic/Capric Triglyceride, Shea Butter Ethyl Esters, Glycerin, Coconut Alkanes, Polyglyceryl-3 Polyricinoleate, Silica, *Simmondsia Chinensis (Jojoba) Seed Oil, Coco-Caprylate/Caprate, Sodium Chloride, Stearalkonium Hectorite, Mica, Polyglyceryl-4 Diisostearate/Polyhydroxystearate/Sebacate, Polyglyceryl-3 Diisostearate, Bisabolol, Phenylpropanol, Lecithin, Propanediol, Allantoin, Caprylyl Glycol, *Terminalia Ferdinandiana Seed Oil, Disodium Acetyl Glucosamine Phosphate, Sodium Glucuronate, Tocopherol (non-GMO), Tetrasodium Glutamate Diacetate, Niacinamide, Magnesium Sulfate, Coffea Arabica (Coffee) Seed Extract, *Calendula Officinalis (Marigold) Flower Extract, Pisum Sativum (Pea) Seed Extract, *Equisetum Arvense (Horsetail) Leaf Extract, *Hypericum Perforatum (St. John’s Wort) Flower Extract, *Curcuma Longa (Turmeric) Root Powder, *Hemidesmus Indicus (Country Sarsaparilla) Root Powder, *Withania Somnifera (Ashwagandha) Root Extract, *Glycyrrhiza Glabra (Licorice) Root, *Olea Europaea (Olive) Leaf, *Aloe Barbadensis Leaf Juice, Benzyl Alcohol, Sodium Hydroxide, Chenopodium Quinoa Seed Extract, Potassium Sorbate, Sodium Benzoate, Caffeine, Titanium Dioxide (CI 77891), Iron Oxides (CI 77491, CI 77492, CI 77499).

*Certified Organic

Hush

Water/Aqua/Eau, Caprylic/Capric Triglyceride, Glycerin, Coconut Alkanes, Polyglyceryl-3 Polyricinoleate, Coco-Caprylate/Caprate, Silica, Shea Butter Ethyl Esters, *Simmondsia Chinensis (Jojoba) Seed Oil, Sodium Chloride, Stearalkonium Hectorite, Mica, Polyglyceryl-4 Diisostearate/Polyhydroxystearate/Sebacate, Polyglyceryl-3 Diisostearate, Bisabolol, Phenylpropanol, Lecithin, Propanediol, Allantoin, Caprylyl Glycol, *Terminalia Ferdinandiana Seed Oil, Disodium Acetyl Glucosamine Phosphate, Sodium Glucuronate, Tocopherol (non-GMO), Tetrasodium Glutamate Diacetate, Niacinamide, Magnesium Sulfate, Coffea Arabica (Coffee) Seed Extract, *Calendula Officinalis (Marigold) Flower Extract, Pisum Sativum (Pea) Seed Extract, *Equisetum Arvense (Horsetail) Leaf Extract, *Hypericum Perforatum (St. John’s Wort) Flower Extract, *Curcuma Longa (Turmeric) Root Powder, *Hemidesmus Indicus (Country Sarsaparilla) Root Powder, *Withania Somnifera (Ashwagandha) Root Extract, *Glycyrrhiza Glabra (Licorice) Root, *Olea Europaea (Olive) Leaf, *Aloe Barbadensis Leaf Juice, Benzyl Alcohol, Sodium Hydroxide, Chenopodium Quinoa Seed Extract, Potassium Sorbate, Sodium Benzoate, Caffeine, Titanium Dioxide (CI 77891), Iron Oxides (CI 77491, CI 77492, CI 77499).

*Certified Organic

Swoon

Water/Aqua/Eau, Caprylic/Capric Triglyceride, Glycerin, Shea Butter Ethyl Esters, Coconut Alkanes, Polyglyceryl-3 Polyricinoleate, Silica, Coco-Caprylate/Caprate, *Simmondsia Chinensis (Jojoba) Seed Oil, Sodium Chloride, Stearalkonium Hectorite, Mica, Polyglyceryl-4 Diisostearate/Polyhydroxystearate/Sebacate, Polyglyceryl-3 Diisostearate, Bisabolol, Phenylpropanol, Lecithin, Propanediol, Allantoin, Caprylyl Glycol, *Terminalia Ferdinandiana Seed Oil, Disodium Acetyl Glucosamine Phosphate, Sodium Glucuronate, Tocopherol (non-GMO), Tetrasodium Glutamate Diacetate, Niacinamide, Magnesium Sulfate, Coffea Arabica (Coffee) Seed Extract, *Calendula Officinalis (Marigold) Flower Extract, Pisum Sativum (Pea) Seed Extract, *Equisetum Arvense (Horsetail) Leaf Extract, *Hypericum Perforatum (St. John’s Wort) Flower Extract, *Curcuma Longa (Turmeric) Root Powder, *Hemidesmus Indicus (Country Sarsaparilla) Root Powder, *Withania Somnifera (Ashwagandha) Root Extract, *Glycyrrhiza Glabra (Licorice) Root, *Olea Europaea (Olive) Leaf, *Aloe Barbadensis Leaf Juice, Benzyl Alcohol, Sodium Hydroxide, Chenopodium Quinoa Seed Extract, Potassium Sorbate, Sodium Benzoate, Caffeine, Titanium Dioxide (CI 77891), Iron Oxides (CI 77491, CI 77492, CI 77499).

*Certified Organic

Company Informataion

dist. by: RMS Organics, LLC. Summerville, SC 29486
made in USA with quality ingredients sourced from around the world

Questions?

www.rmsbeauty.com